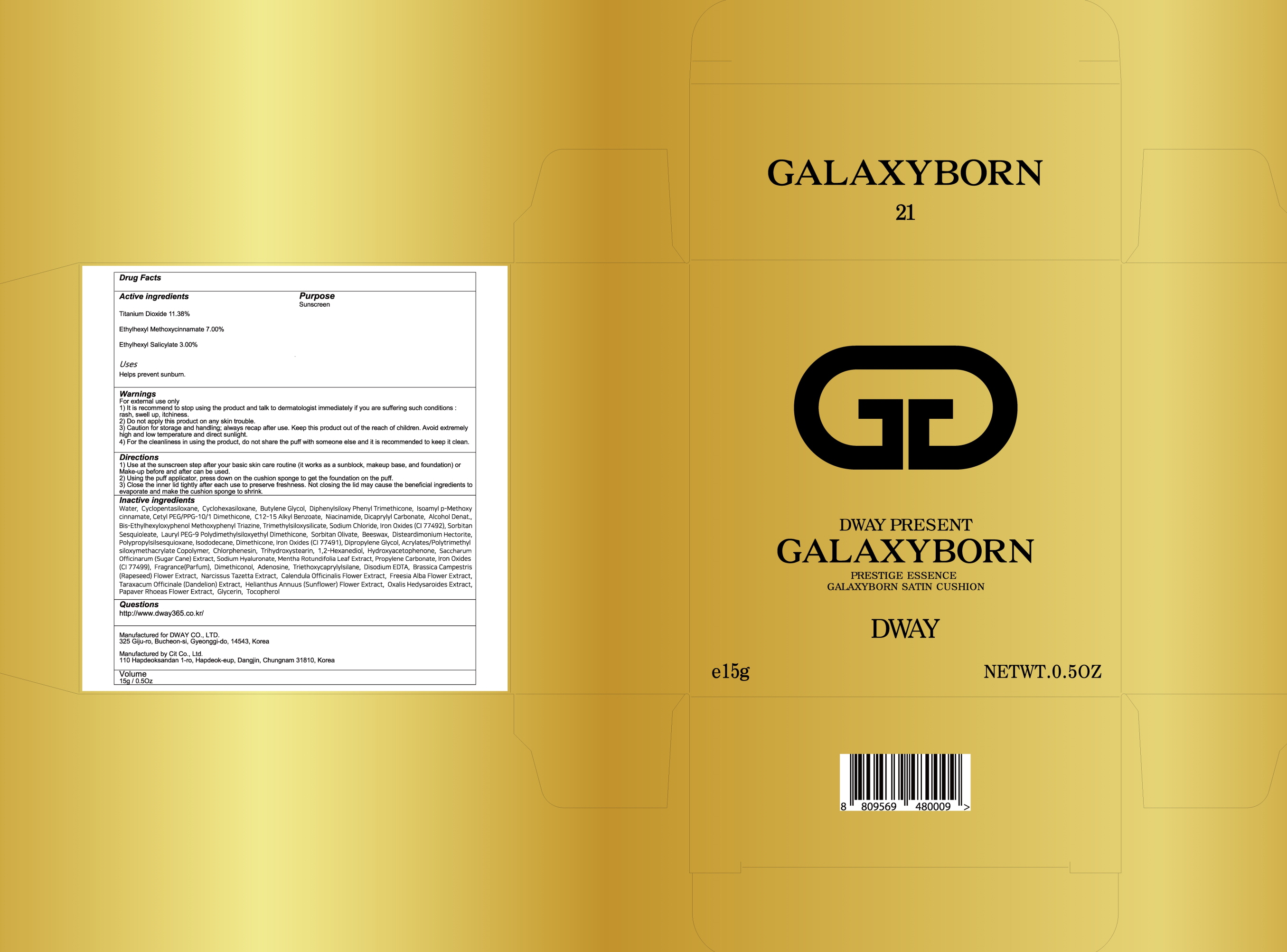 DRUG LABEL: GALAXYBORN SATIN CUSHION NO 21
NDC: 72256-010 | Form: POWDER
Manufacturer: DWAY CO LTD
Category: otc | Type: HUMAN OTC DRUG LABEL
Date: 20190328

ACTIVE INGREDIENTS: Titanium Dioxide 1.70 g/15 g; Octinoxate 1.05 g/15 g; Octisalate 0.45 g/15 g
INACTIVE INGREDIENTS: Water; Butylene Glycol

ACTIVE INGREDIENT

Active ingredients: Titanium Dioxide 11.38%, Ethylhexyl Methoxycinnamate 7.00%, Ethylhexyl Salicylate 3.00%

INACTIVE INGREDIENT

Inactive ingredients:

Water, Cyclopentasiloxane, Cyclohexasiloxane, Butylene Glycol, Diphenylsiloxy Phenyl Trimethicone, Isoamyl p-Methoxycinnamate, Cetyl PEG/PPG-10/1 Dimethicone, C12-15 Alkyl Benzoate, Niacinamide, Dicaprylyl Carbonate, Alcohol Denat., Bis-Ethylhexyloxyphenol Methoxyphenyl Triazine, Trimethylsiloxysilicate, Sodium Chloride, Iron Oxides (CI 77492), Sorbitan Sesquioleate, Lauryl PEG-9 Polydimethylsiloxyethyl Dimethicone, Sorbitan Olivate, Beeswax, Disteardimonium Hectorite, Polypropylsilsesquioxane, Isododecane, Dimethicone, Iron Oxides (CI 77491), Dipropylene Glycol, Acrylates/Polytrimethylsiloxymethacrylate Copolymer, Chlorphenesin, Trihydroxystearin, 1,2-Hexanediol, Hydroxyacetophenone, Saccharum Officinarum (Sugar Cane) Extract, Sodium Hyaluronate, Mentha Rotundifolia Leaf Extract, Propylene Carbonate, Iron Oxides (CI 77499), Fragrance(Parfum), Dimethiconol, Adenosine, Triethoxycaprylylsilane, Disodium EDTA, Brassica Campestris (Rapeseed) Flower Extract, Narcissus Tazetta Extract, Calendula Officinalis Flower Extract, Freesia Alba Flower Extract, Taraxacum Officinale (Dandelion) Extract, Helianthus Annuus (Sunflower) Flower Extract, Oxalis Hedysaroides Extract, Papaver Rhoeas Flower Extract, Glycerin, Tocopherol

PURPOSE

Purpose: Sunscreen

WARNINGS

For external use only
1) It is recommend to stop using the product and talk to dermatologist immediately if you are suffering such conditions : rash, swell up, itchiness.
2) Do not apply this product on any skin trouble.
3) Caution for storage and handling; always recap after use. Keep this product out of the reach of children. Avoid extremely high and low temperature and direct sunlight.
4) For the cleanliness in using the product, do not share the puff with someone else and it is recommended to keep it clean.

DESCRIPTION

Uses:
Helps prevent sunburn.

Directions:
1) Use at the sunscreen step after your basic skin care routine (it works as a sunblock, makeup base, and foundation) or Make-up before and after can be used.
2) Using the puff applicator, press down on the cushion sponge to get the foundation on the puff.
3) Close the inner lid tightly after each use to preserve freshness. Not closing the lid may cause the beneficial ingredients to evaporate and make the cushion sponge to shrink.